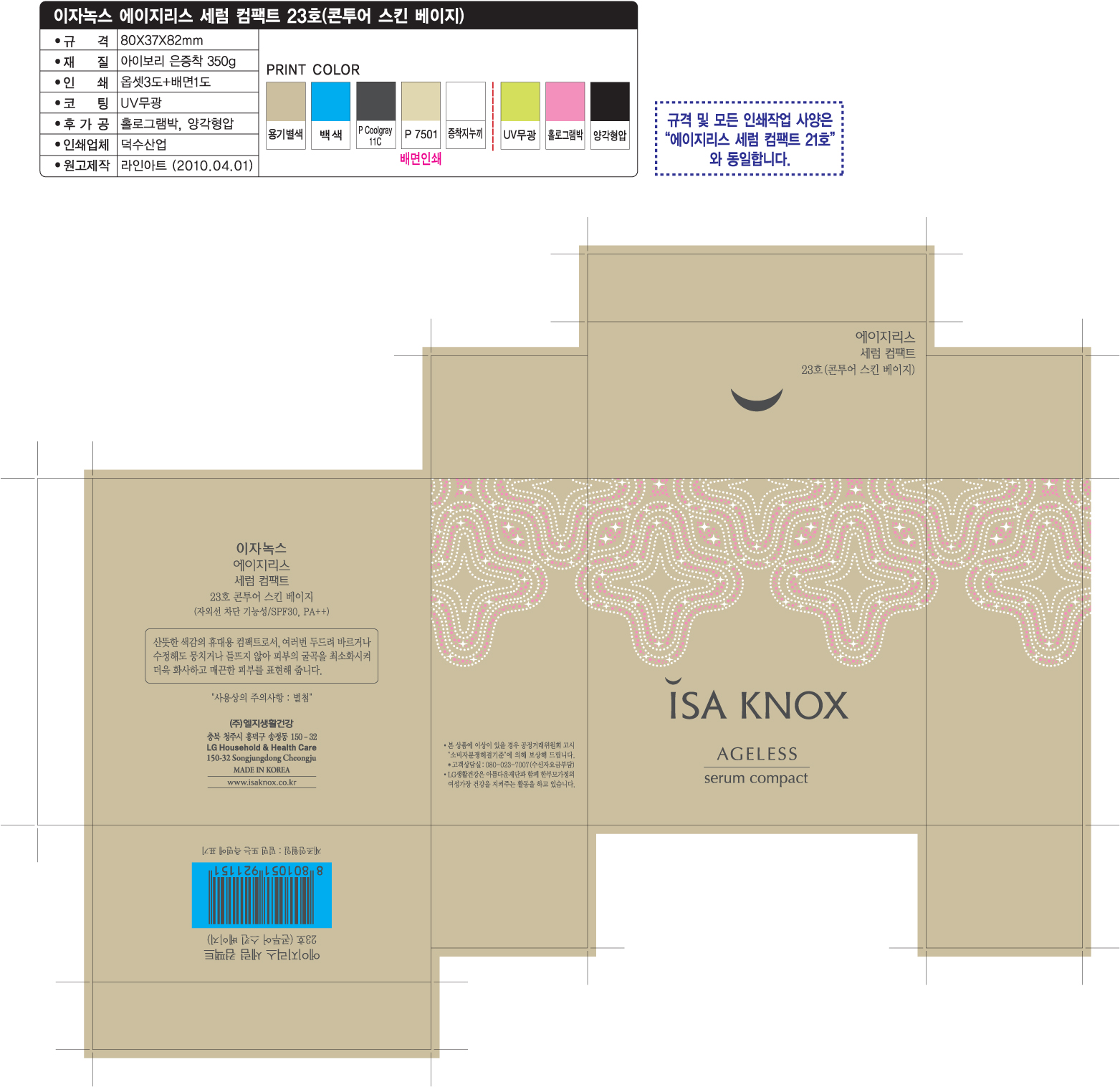 DRUG LABEL: ISAKNOX AGELESS SERUM COMPACT 23
NDC: 53208-480 | Form: POWDER
Manufacturer: LG Household and Healthcare, Inc. 
Category: otc | Type: HUMAN OTC DRUG LABEL
Date: 20120515

ACTIVE INGREDIENTS: TITANIUM DIOXIDE 4.9 g/100 g; OCTINOXATE 2 g/100 g
INACTIVE INGREDIENTS: TALC; ALUMINUM STARCH OCTENYLSUCCINATE; SILICON DIOXIDE; MAGNESIUM STEARATE; MAGNESIUM; METHYLPARABEN; PROPYLPARABEN; DIMETHICONE

Drug Fact

Active Ingredients

TITANIUM DIOXIDE 4.9g/100g

OCTINOXATE 2g/100g

Warning and Precautions

For external use only.

Keep out of reach of children. Is swallowed, get medical help or contact a Poison Control Center right away.

WHEN USING

Keep out of eyes. Rinse with water to remove.

PACKAGE LABEL

Isaknox
Ageless

Serum Compact 23